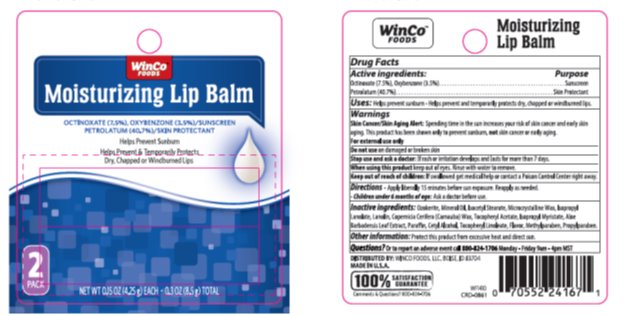 DRUG LABEL: Winco Moisture SPF 15 Lip Balm
NDC: 67091-250 | Form: STICK
Manufacturer: Winco
Category: otc | Type: HUMAN OTC DRUG LABEL
Date: 20220117

ACTIVE INGREDIENTS: OCTINOXATE 7.5 mg/1 g; OXYBENZONE 3.5 mg/1 g; PETROLATUM 40.7 mg/1 g
INACTIVE INGREDIENTS: CERESIN 17.13 mg/1 g; LIGHT MINERAL OIL 16.75 mg/1 g; ISOCETYL STEARATE 3.50 mg/1 g; MICROCRYSTALLINE WAX 3.00 mg/1 g; LANOLIN 1 mg/1 g; .ALPHA.-TOCOPHEROL ACETATE .60 mg/1 g

Drug Facts

Active ingredient

Octinoxate (7.5%), Oxybenzone (3.5%)

Petrolatum (40.7%)

Purpose

Sunscreen, Sunscreen, Skin Protectant

Keep Out of Reach of Children

If swallowed get medical help or contact a Poison Control Center right away.

Uses

Helps prevent sunburn. Helps prevent and temporarily protects dry, chapped or windburned lips.

Warnings

Skin Cancer/Skin Aging Alert: Spending time in the sun increases your risk of skin cancer and early skin aging. This product has been shown only to prevent sunburn, not skin cancer or early aging.

For external use only

Do not use on broken or damaged skin

Stop use and ask a doctor: If rash or irritation develops and lasts for more than 7 days.

When using this product keep out of eyes. Rinse with water to remove.

Directions

Apply liberally 15 minutes before sun exposure. Reapply as needed.

Children under 6 months of age: Ask a doctor before use.

Inactive Ingredients

Ozokerite, Mineral Oil, Isocetyl Stearate, Microcrystalline Wax, Isopropyl Lanolate, Lanolin, Copernicia Cerifera (Carnauba) Wax, Tocopheryl Acetate, Isopropyl Myristate, Aloe Barbadenis Leaf Extract, Paraffin, Cetyl Alcohol, Tocerpheryl Linoleate, Flavor, Methylparaben, Propylparaben.